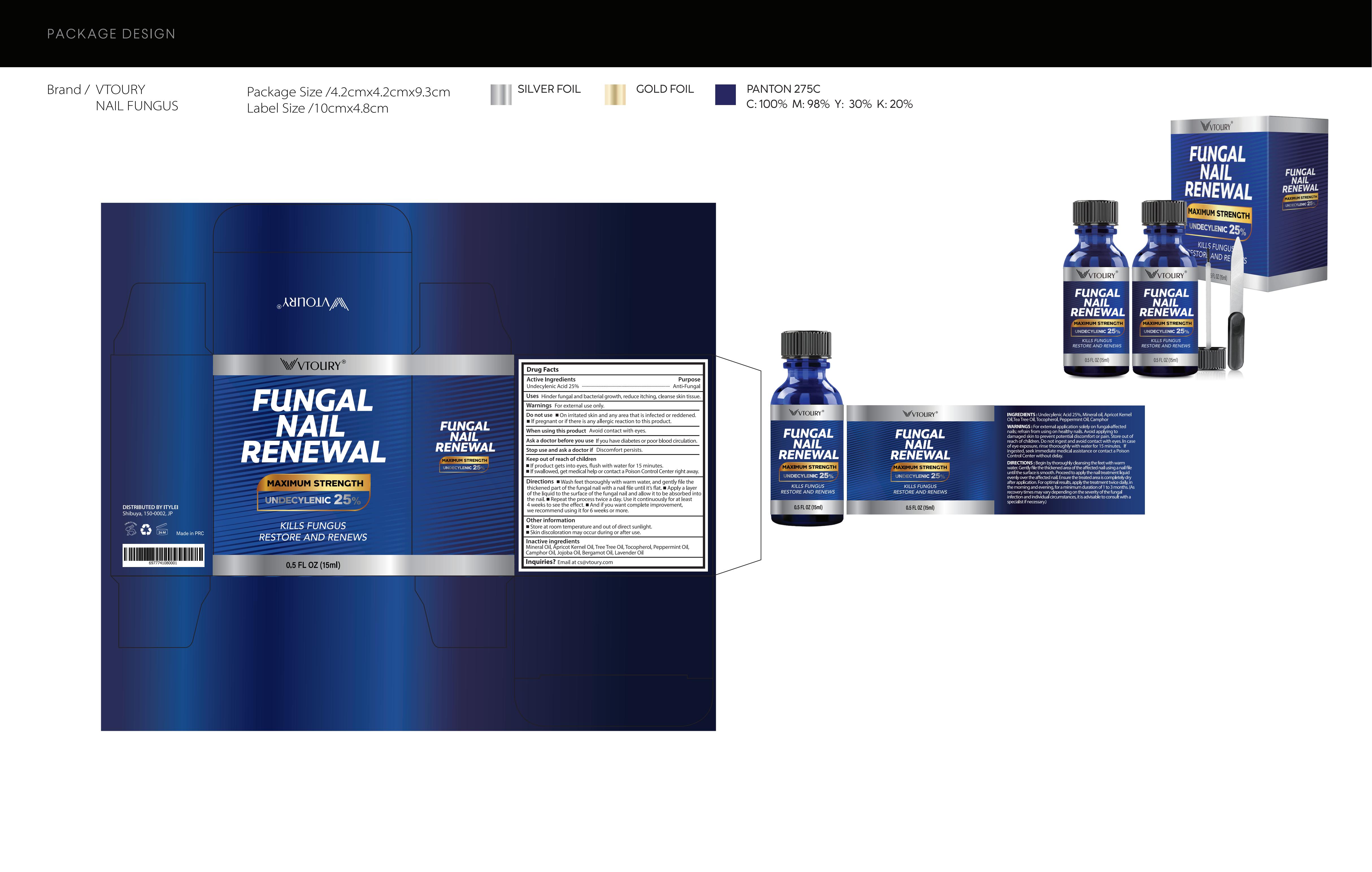 DRUG LABEL: VTROUY Fungus Nail Renewal
NDC: 85817-007 | Form: LIQUID
Manufacturer: Guangzhou Qiexiran Cosmetics Co., Ltd.
Category: otc | Type: HUMAN OTC DRUG LABEL
Date: 20251015

ACTIVE INGREDIENTS: UNDECYLENIC ACID 25 g/100 mL
INACTIVE INGREDIENTS: LAVENDER OIL; TEA TREE OIL; TOCOPHEROL; CAMPHOR OIL; JOJOBA OIL; BERGAMOT OIL; PEPPERMINT OIL; MINERAL OIL; APRICOT KERNEL OIL

85817-007

Active Ingredient

Undecylenic Acid 25%

Purpose

Antifungal

Use

Hinder fungal and bacterial growth, reduce itching, cleanse skin tissue.

Warnings

For external use only.

Do not use

On irritated skin and any area that is infected or reddened. If pregnant or if there is any allergic reaction to this product.

When Using

Avoid contact with eyes.

Stop Use

Stop use and ask a doctor If discomfort persists.

Ask Doctor

If you have diabetes or poor blood circulation.

Keep Out Of Reach Of Children

If product gets into eyes, flush with water for 15 minutes.
If swallowed, get medical help or contact a Poison Control Center right away.

Directions

Wash feet thoroughly with warm water, and gently file the thickened part of the fungal nail with a nail file until it's flat.
Apply a layer of the liquid to the surface of the fungal nail and allow it to be absorbed into the nail.
Repeat the process twice a day. Use it continuously for at least 4 weeks to see the effect. And if you want complete improvement, we recommend using it for 6 weeks or more.

Other information

Store at room temperature and out of direct sunlight.
Skin discoloration may occur during or after use.

Inactive ingredients

Mineral oil, Apricot Kernel Oil, Tea Tree Oil, Tocopherol, Peppermint Oil, Camphor Oil, Jojoba Oil, Bergamot Oil, Lavender Oil.

Questions

Email at cs@vtoury.com